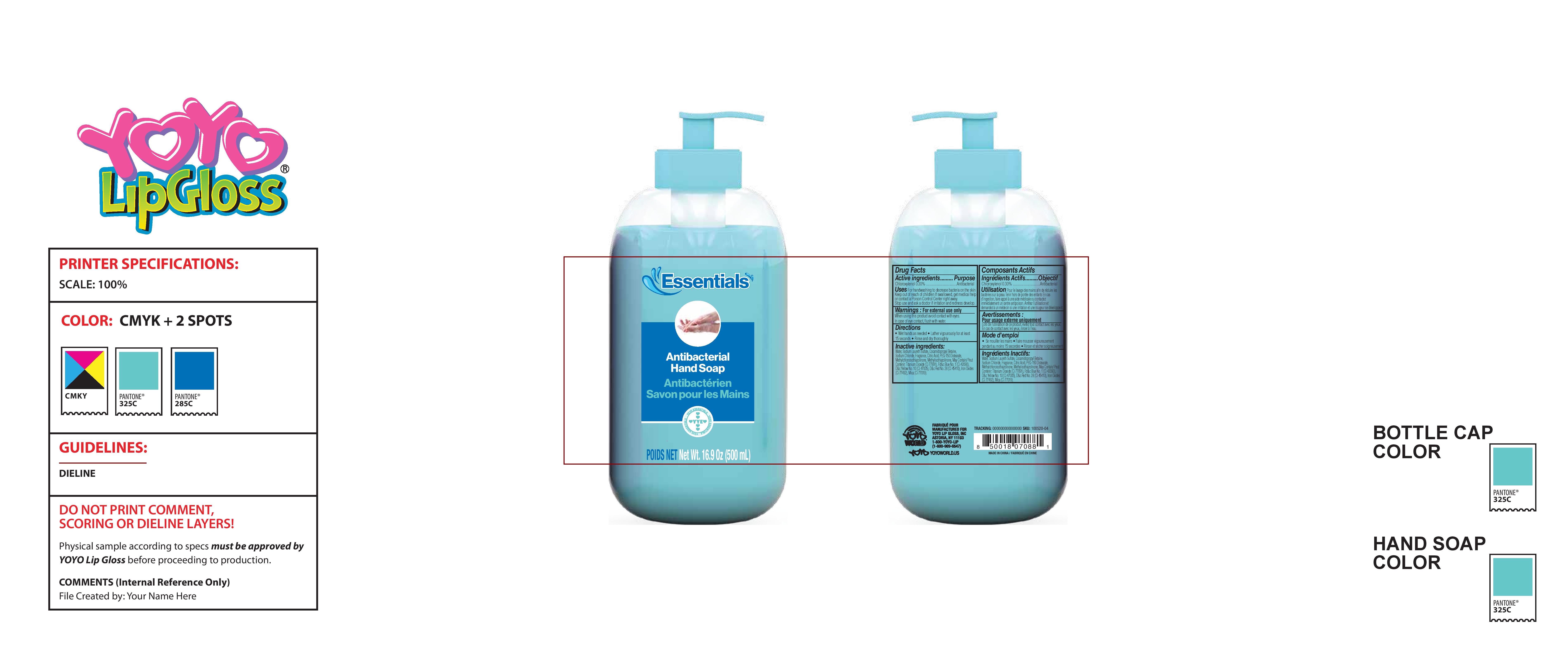 DRUG LABEL: Handsoap
NDC: 70611-555 | Form: SOAP
Manufacturer: YOYO LIP GLOSS, INC
Category: otc | Type: HUMAN OTC DRUG LABEL
Date: 20201012

ACTIVE INGREDIENTS: CHLOROXYLENOL 0.3 g/100 mL
INACTIVE INGREDIENTS: SODIUM CHLORIDE; TITANIUM DIOXIDE; FD&C BLUE NO. 1; METHYLCHLOROISOTHIAZOLINONE; WATER; COCAMIDOPROPYL BETAINE; MICA; CITRIC ACID ACETATE; PEG-150 DISTEARATE; METHYLISOTHIAZOLINONE; BROWN IRON OXIDE; D&C RED NO. 28; D&C YELLOW NO. 10; SODIUM LAURETH SULFATE; FRAGRANCE CLEAN ORC0600327

ACTIVE INGREDIENT

Chloroxylenol 0.30% v/v Purpose: Antibacterial

INDICATIONS AND USAGE

For handwashing to decrease bacteria on the skin

WARNINGS

For external use only. When using this product, avoid contact with eyes. In case of eye contact, flush with water.

Keep out of reach of children

If swallowed, get medical help or contact poison control center right away

Stop use and ask doctor if irritation and redness develop

Keep out of reach of children

If swallowed, get medical help or contact a Poison Control Center right away.

DOSAGE AND ADMINISTRATION

Wet hands as needed

Lather vigourously for at least 15 seconds

Rinse and dry thoroughly

INACTIVE INGREDIENT

water, sodium laureth sulfate, cocamidopropyl betaine, sodium chloride, fragrance, citric acid, peg-15 distearate, methylchloroisothiazolinone, methylisothiazolinone, may contain: titanium dioxide (Ci 77891), Fd&c Blue No. 1 (Ci 42090), D&c Yellow No. 10 (Ci 47005), D&c Red No. 28 (Ci 45410), Iron Oxides (Ci 77492), Mica (Ci 77019)